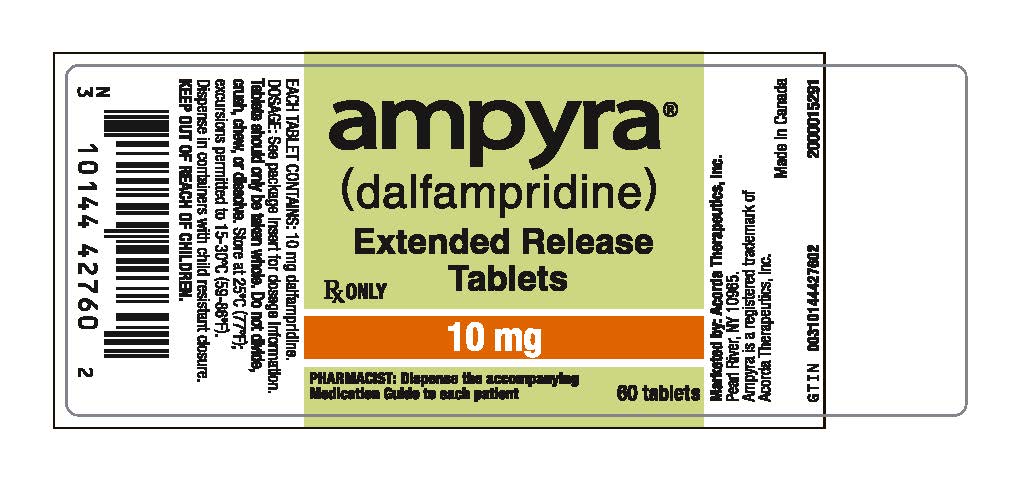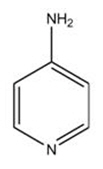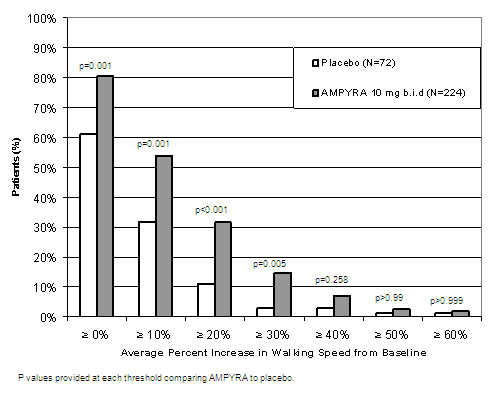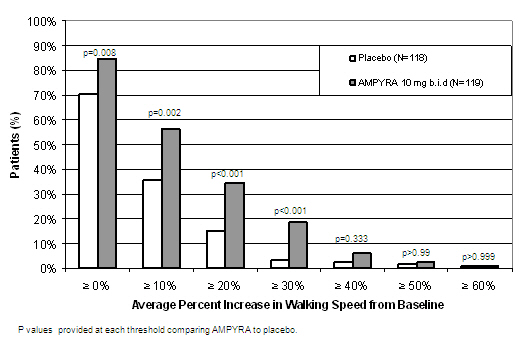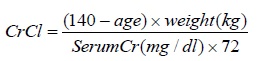 DRUG LABEL: AMPYRA
NDC: 10144-427 | Form: TABLET, FILM COATED, EXTENDED RELEASE
Manufacturer: Merz Pharmaceuticals, LLC
Category: prescription | Type: HUMAN PRESCRIPTION DRUG LABEL
Date: 20260116

ACTIVE INGREDIENTS: DALFAMPRIDINE 10 mg/1 1
INACTIVE INGREDIENTS: HYPROMELLOSE, UNSPECIFIED; SILICON DIOXIDE; MICROCRYSTALLINE CELLULOSE; MAGNESIUM STEARATE; TITANIUM DIOXIDE; POLYETHYLENE GLYCOL, UNSPECIFIED

HIGHLIGHTS OF PRESCRIBING INFORMATION

These highlights do not include all the information needed to use AMPYRA safely and effectively. See full prescribing information for AMPYRA.
AMPYRA ® (dalfampridine) extended-release tablets, for oral use
Initial U.S. Approval: 2010

1 INDICATIONS AND USAGE

AMPYRA ® (dalfampridine) is a potassium channel blocker indicated to improve walking in adult patients with multiple sclerosis (MS). This was demonstrated by an increase in walking speed (1, 14).

2 DOSAGE AND ADMINISTRATION

- The maximum recommended dosage is 10 mg twice daily (approximately 12 hours apart). There is no evidence of additional benefit with doses greater than 10 mg twice daily. Adverse reactions, including seizures, were more frequent at higher doses. (2.1)
- Take with or without food. Administer tablets whole; do not divide, crush, chew, or dissolve (2.2)
- Patients should not take double or extra doses if they miss a dose. (2.2)
- Estimated creatinine clearance (CrCl) should be known before initiating treatment with AMPYRA. In patients with mild renal impairment (CrCl 51–80 mL/min), AMPYRA may reach plasma levels associated with a greater risk of seizures, and the potential benefits of AMPYRA should be carefully considered against the risk of seizures in these patients (2.3, 5.2, 8.6)

3 DOSAGE FORMS AND STRENGTHS

10 mg tablets (3)

4 CONTRAINDICATIONS

- History of seizure (4)
- Moderate or severe renal impairment (CrCl≤50 mL/min) (4)
- History of hypersensitivity to AMPYRA or 4-aminopyridine (4)

5 WARNINGS AND PRECAUTIONS

- AMPYRA can cause seizures; the risk of seizures increases with increasing AMPYRA doses; discontinue AMPYRA and do not restart if a seizure occurs (5.1)
- Avoid concomitant use with other forms of 4-aminopyridine (4-AP, fampridine), since the active ingredient is the same (5.3)
- AMPYRA can cause anaphylaxis. Discontinue and do not restart AMPYRA if this occurs (5.4)

6 ADVERSE REACTIONS

The most common adverse events (incidence ≥2% and at a rate greater than the placebo rate) for AMPYRA were urinary tract infection, insomnia, dizziness, headache, nausea, asthenia, back pain, balance disorder, multiple sclerosis relapse, paresthesia, nasopharyngitis, constipation, dyspepsia, and pharyngolaryngeal pain (6.1).
To report SUSPECTED ADVERSE REACTIONS, contact Acorda Therapeutics at 1-800-367-5109 or FDA at 1-800-FDA-1088 or www.fda.gov/medwatch.

7 DRUG INTERACTIONS

OCT2 Inhibitors: Concomitant use may cause an increased exposure and potential risk of seizures (7.1)

8 USE IN SPECIFIC POPULATIONS

- Pregnancy: Based on animal data, may cause fetal harm (8.1)
- Geriatric use: Because elderly patients are more likely to have decreased renal function, it is particularly important to know the estimated CrCl in these patients before initiating AMPYRA treatment (4, 5.2, 8.6)

FULL PRESCRIBING INFORMATION

1 INDICATIONS AND USAGE

AMPYRA is indicated as a treatment to improve walking in adult patients with multiple sclerosis (MS). This was demonstrated by an increase in walking speed [see Clinical Studies (14)].

2 DOSAGE AND ADMINISTRATION

2.1 Dosage Information

The maximum recommended dosage of AMPYRA is one 10 mg tablet twice daily and should not be exceeded. Take doses approximately 12 hours apart.

There is no evidence of additional benefit at doses greater than 10 mg twice daily. Adverse reactions, including seizures, and discontinuations because of adverse reactions were more frequent at higher doses.

2.2 Administration Instructions

AMPYRA can be taken with or without food. Administer tablets whole; do not divide, crush, chew, or dissolve AMPYRA tablets.

If a dose is missed, patients should not take double or extra doses.

2.3 Renal Monitoring Prior to and During Treatment

Estimated creatinine clearance (CrCl) should be known before initiating treatment with AMPYRA, and monitored at least annually during treatment with AMPYRA. CrCl can be estimated using the following equation (multiply by 0.85 for women):

2.4 Dosage in Patients with Renal Impairment

In patients with mild renal impairment (CrCl 51–80 mL/min), AMPYRA plasma levels may approach those seen at a dose of 15 mg twice daily, a dose that is 1.5 times the maximum recommended dose and may be associated with an increased risk of seizures. As mild renal impairment is common after age 50, estimating CrCl is particularly important in these patients. The potential benefits of AMPYRA should be carefully considered against the risk of seizures in these patients [see Warnings and Precautions (5.2) and Clinical Pharmacology (12.3)]. AMPYRA is contraindicated in patients with moderate or severe renal impairment (CrCl≤50 mL/min).

3 DOSAGE FORMS AND STRENGTHS

AMPYRA is available in a 10 mg strength and is a film-coated, white to off-white, biconvex, oval shaped, non-scored tablet with flat edge, debossed with "A10" on one side.

4 CONTRAINDICATIONS

The use of AMPYRA is contraindicated in the following conditions:

- History of seizure [see Warnings and Precautions (5.1)]
- Moderate or severe renal impairment (CrCl≤50 mL/min) [see Warnings and Precautions (5.2)]
- History of hypersensitivity to AMPYRA or 4-aminopyridine; reactions have included anaphylaxis [see Warnings and Precautions (5.4)]

5 WARNINGS AND PRECAUTIONS

5.1 Seizures

AMPYRA can cause seizures. Increased incidence of seizures has been observed at 20 mg twice daily (2 times the maximum recommended dosage) in controlled clinical studies of 9–14 weeks duration with dalfampridine in patients with MS. In open-label extension trials in MS patients, the incidence of seizures during treatment with dalfampridine 15 mg twice daily (1.7/100PY) was over 4 times higher than the incidence during treatment with 10 mg twice daily (0.4/100PY). In the post-marketing period seizures have been reported. The majority of seizures occurred at the recommended dose and in patients without a history of seizures, and generally within days to weeks of starting therapy.

AMPYRA has not been evaluated in patients with a history of seizures or with evidence of epileptiform activity on an EEG, as these patients were excluded from clinical trials. The risk of seizures in patients with epileptiform activity on an EEG is unknown, and could be substantially higher than that observed in AMPYRA clinical studies. Permanently discontinue AMPYRA in patients who have a seizure while on treatment. AMPYRA is contraindicated in patients with a history of seizures [see Contraindications (4)] .

5.2 Renal Impairment

AMPYRA is eliminated through the kidneys primarily as unchanged drug [see Clinical Pharmacology (12.3)].

Because patients with moderate to severe renal impairment (CrCl ≤50mL/min) would require a dose lower than 10 mg twice daily and no strength smaller than 10 mg is available, AMPYRA is contraindicated in these patients [see Contraindications (4)] .

In patients with mild renal impairment (CrCl 51–80 mL/min), AMPYRA plasma levels may approach those seen at a dose of 15 mg twice daily, a dose that may be associated with an increased risk of seizures [see Warnings and Precautions (5.1)] .

5.3 Concurrent Treatment with Other Forms of 4-Aminopyridine

Avoid concomitant use with other forms of 4-aminopyridine (4-AP, fampridine) since the active ingredient is the same. Instruct patients to discontinue use of any product containing 4-aminopyridine prior to initiating treatment with AMPYRA in order to reduce the potential for dose-related adverse reactions.

5.4 Anaphylaxis

AMPYRA can cause anaphylaxis and severe allergic reactions. Signs and symptoms have included respiratory compromise, urticaria, and angioedema of the throat and or tongue. AMPYRA is contraindicated in patients with a history of hypersensitivity to AMPYRA or 4-aminopyridine. Inform patients of the signs and symptoms of anaphylaxis and instruct them to discontinue AMPYRA and seek immediate medical care should these signs and symptoms occur.

6 ADVERSE REACTIONS

The following serious adverse reactions are described in more detail elsewhere in the labeling:

- Seizures [see Warnings and Precautions (5.1)]
- Anaphylaxis [see Warnings and Precautions (5.4)]

6.1 Clinical Trials Experience

Because clinical studies are conducted under widely varying conditions, adverse reaction rates observed in the clinical studies of a drug cannot be directly compared to rates in the clinical studies of another drug and may not reflect the rates observed in practice.

In three placebo-controlled clinical trials of up to 14 weeks duration, 4% (15/400) of patients treated with AMPYRA 10 mg twice daily experienced one or more adverse reactions leading to discontinuation, compared to 2% (5/238) of placebo-treated patients. The adverse reactions leading to discontinuation of at least 2 patients treated with AMPYRA and that led to discontinuation more frequently compared to placebo were headache (AMPYRA 0.5%, placebo 0%), balance disorder (AMPYRA 0.5%, placebo 0%), dizziness (AMPYRA 0.5%, placebo 0%), and confusional state (AMPYRA 0.3%, placebo 0%).

Table 1 lists adverse reactions that occurred in ≥2% of patients treated with AMPYRA 10 mg twice daily, and more frequently than in placebo-treated patients, in controlled clinical trials.

Table 1: Adverse Reactions with an Incidence ≥2% of AMPYRA-Treated Adult MS Patients and More Frequent with AMPYRA Compared to Placebo in Controlled Clinical Trials
Adverse Reaction | Placebo (N=238); % | AMPYRA 10 mg twice daily (N=400); %
Urinary tract infection | 8 | 12
Insomnia | 4 | 9
Dizziness | 4 | 7
Headache | 4 | 7
Nausea | 3 | 7
Asthenia | 4 | 7
Back pain | 2 | 5
Balance disorder | 1 | 5
Multiple sclerosis relapse | 3 | 4
Paresthesia | 3 | 4
Nasopharyngitis | 2 | 4
Constipation | 2 | 3
Dyspepsia | 1 | 2
Pharyngolaryngeal pain | 1 | 2

Other Adverse Reactions

AMPYRA has been evaluated in a total of 1,952 subjects, including 917 MS patients. A total of 741 patients have been treated with AMPYRA for over six months, 501 for over one year and 352 for over two years. The experience in open-label clinical trials is consistent with the safety profile observed in the placebo-controlled clinical trials. As in controlled clinical trials, a dose-dependent increase in the incidence of seizures has been observed in open-label clinical trials with AMPYRA in patients with MS as follows: AMPYRA 10 mg twice daily 0.41 per 100 person-years (95% confidence interval 0.13–0.96); dalfampridine 15 mg twice daily 1.7 per 100 person-years (95% confidence interval 0.21–6.28).

6.2 Postmarketing Experience

The following adverse reactions have been identified during post approval use with dalfampridine. Because these reactions are reported voluntarily from a population of uncertain size, it is not always possible to reliably estimate their frequency or establish a causal relationship to drug exposure: vomiting, vertigo.

7 DRUG INTERACTIONS

7.1 OCT2 Inhibitors

Concurrent treatment with OCT2 inhibitors, such as cimetidine, may cause increased exposure to dalfampridine [see Clinical Pharmacology (12.3)]. Elevated levels of dalfampridine increase the risk of seizures [see Warnings and Precautions (5.1, 5.2)]. The potential benefits of taking OCT2 inhibitors concurrently with AMPYRA should be considered against the risk of seizures in these patients.

7.2 Baclofen

No interaction was identified between dalfampridine and baclofen [see Clinical Pharmacology (12.3)].

8 USE IN SPECIFIC POPULATIONS

8.1 Pregnancy

Risk Summary

There are no adequate data on the developmental risk associated with use of AMPYRA in pregnant women. Administration of dalfampridine to animals during pregnancy and lactation resulted in decreased offspring viability and growth at clinically relevant doses [see Data]. In the U.S. general population, the estimated background risk of major birth defects and miscarriage in clinically recognized pregnancies is 2 to 4% and 15 to 20%, respectively. The background risk of major birth defects and miscarriage for the indicated population is unknown.

Data

Animal Data

Oral administration of dalfampridine to pregnant rats and rabbits throughout organogenesis resulted in no evidence of developmental toxicity in either species. The highest doses tested (10 mg/kg/day in rats, 5 mg/kg/day in rabbits), which were associated with maternal toxicity, are approximately 5 times the MRHD on a body surface area (mg/m^2) basis.

Oral administration of dalfampridine (0, 1, 3, and 9 to 6 mg/kg/day; high dose reduced during the second week of dosing) to female rats throughout pregnancy and lactation resulted in decreased offspring viability at the highest dose tested and decreased body weight in offspring at the mid and high doses. The no-effect dose for pre- and postnatal developmental toxicity in rats (1 mg/kg/day) is less than the MRHD on a mg/m^2 basis.

8.2 Lactation

Risk Summary

There are no data on the presence of dalfampridine in human milk, the effects of dalfampridine on the breastfed infant, or the effects on milk production. The developmental and health benefits of breastfeeding should be considered along with the mother's clinical need for AMPYRA and any potential adverse effects on the breastfed infant from AMPYRA or from the underlying maternal condition.

8.4 Pediatric Use

Safety and effectiveness in patients younger than 18 years of age have not been established.

8.5 Geriatric Use

Clinical studies of AMPYRA did not include sufficient numbers of subjects aged 65 and over to determine whether they respond differently than younger subjects. A population PK analysis showed that dalfampridine clearance modestly decreased with increasing age, but not sufficiently to necessitate a modification of dose with age. Other reported clinical experience has identified no differences in responses between the elderly and younger patients.

AMPYRA is known to be substantially excreted by the kidneys and the risk of adverse reactions, including seizures, is greater with increasing exposure of dalfampridine. Because elderly patients are more likely to have decreased renal function, it is particularly important to know the estimated creatinine clearance (CrCl) in these patients [see Warnings and Precautions (5.2)].

8.6 Impaired Renal Function

Clearance of dalfampridine is decreased in patients with renal impairment and is significantly correlated with creatinine clearance (CrCl) [see Clinical Pharmacology (12.3)]. AMPYRA is contraindicated in patients with moderate or severe renal impairment (CrCl ≤50 mL/min) [see Contraindications (4)]. The risk of seizures in patients with mild renal impairment (CrCl 51–80 mL/min) is unknown, but dalfampridine plasma levels in these patients may approach those seen at a dose of 15 mg twice daily, a dose that may be associated with an increased risk of seizures. If unknown, estimated creatinine clearance should be calculated prior to initiating treatment with AMPYRA [see Dosage and Administration (2.3) and Warnings and Precautions (5.2)] .

10 OVERDOSAGE

Three cases of overdose were reported in controlled clinical trials with AMPYRA, involving two MS patients. The first patient took six times the currently recommended dose (60 mg) and was taken to the emergency room with altered mental state. The second patient took 40 mg doses on two separate occasions. In the first instance, she experienced a complex partial seizure and, in the second instance, a period of confusion. Both patients recovered by the following day without sequelae.

Several cases of overdose are found in the scientific literature in which various formulations of dalfampridine were used, resulting in numerous adverse events including seizure, confusion, tremulousness, diaphoresis, and amnesia. In some instances, patients developed status epilepticus, requiring intensive supportive care and were responsive to standard therapy for seizures. In one published case report, an MS patient who ingested 300 mg of 4-aminopyridine (dalfampridine) developed a condition that resembled limbic encephalitis. This patient developed weakness, reduced awareness, memory loss, hypophonic speech, and temporal lobe hyperintensities on MRI. The patient's speech and language and ambulation improved over time, and an MRI at 4 months after the overdose no longer showed signal abnormalities. At one year, the patient continued to have difficulty with short term memory and learning new tasks.

11 DESCRIPTION

AMPYRA (dalfampridine) is a potassium channel blocker, available in a 10 mg tablet strength. Each tablet contains 10 mg dalfampridine, formulated as an extended-release tablet for twice-daily oral administration. Dalfampridine is also known by its chemical name, 4-aminopyridine, with the following structure:

AMPYRA (dalfampridine) extended-release tablets are available in a 10 mg strength and are white to off-white, biconvex, oval shaped, film-coated, non-scored tablets with flat edge, debossed with "A10" on one side, containing 10 mg of dalfampridine. Inactive ingredients consist of colloidal silicon dioxide, hydroxypropyl methylcellulose, magnesium stearate, microcrystalline cellulose, polyethylene glycol, and titanium dioxide.

Dalfampridine is a fine white powder with a molecular weight of 94.1, CAS 504-24-5, and a molecular formula of C 5H 6N 2. At ambient conditions, dalfampridine is soluble in water, methanol, acetone, tetrahydrofuran, isopropanol, acetonitrile, N,N-dimethylformamide, dimethylsulfoxide, and ethanol.

12 CLINICAL PHARMACOLOGY

12.1 Mechanism of action

The mechanism by which dalfampridine exerts its therapeutic effect has not been fully elucidated. Dalfampridine is a broad spectrum potassium channel blocker. In animal studies, dalfampridine has been shown to increase conduction of action potentials in demyelinated axons through inhibition of potassium channels.

12.2 Pharmacodynamics

AMPYRA does not prolong the QTc interval and does not have a clinically important effect on QRS duration.

12.3 Pharmacokinetics

Absorption and Distribution

Orally administered dalfampridine is rapidly and completely absorbed from the gastrointestinal tract. Absolute bioavailability of extended release AMPYRA tablets has not been assessed, but relative bioavailability is 96% when compared to an aqueous oral solution. The extended release tablet delays absorption of dalfampridine relative to the solution formulation, giving a slower rise to a lower peak concentration (Cmax), with no effect on the extent of absorption (AUC). Single AMPYRA tablet 10 mg doses administered to healthy volunteers in a fasted state gave peak concentrations ranging from 17.3 ng/mL to 21.6 ng/mL occurring 3 to 4 hours post-administration (Tmax). In comparison, Cmax with the same 10 mg dose of dalfampridine in an oral solution was 42.7 ng/mL and occurred approximately 1.3 hours after dosing. Exposure increased proportionally with dose.

Dalfampridine is largely unbound to plasma proteins (97–99%). The apparent volume of distribution is 2.6 L/kg.

There is no apparent difference in pharmacokinetic parameter values following administration of AMPYRA tablets to either healthy volunteers or patients with MS.

When dalfampridine is taken with food, there is a slight increase in Cmax (12–17%) and a slight decrease in AUC (4–7%). These changes in exposure are not clinically significant, and therefore the drug may be taken with or without food [see Dosage and Administration (2.2)].

Metabolism and Elimination

Dalfampridine and metabolites elimination is nearly complete after 24 hours, with 95.9% of the dose recovered in urine and 0.5% recovered in feces. Most of the excreted radioactivity in urine was parent drug (90.3%). Two metabolites were identified: 3-hydroxy-4-aminopyridine (4.3%) and 3-hydroxy-4-aminopyridine sulfate (2.6%). These metabolites have been shown to have no pharmacologic activity on potassium channels.

The apparent elimination half-life of dalfampridine following administration of the extended release tablet formulation of AMPYRA is 5.2 to 6.5 hours. The plasma half-life of the sulfate conjugate is approximately 7.6 hours and the half-life of 3-hydroxy-4-aminopyridine could not be calculated because concentrations for most subjects were close to or below the limit of quantitation.

In vitro studies with human liver microsomes indicate that CYP2E1 was the major enzyme responsible for the 3-hydroxylation of dalfampridine. The identity of the CYP enzymes suspected of playing a minor role in the 3-hydroxylation of dalfampridine could not be established unequivocally.

Specific Populations

Pediatric

The safety and effectiveness in patients younger than 18 years of age have not been established.

Geriatric

A population pharmacokinetic analysis showed that dalfampridine clearance modestly decreased with increasing age, but not sufficiently to necessitate a modification of dose.

Gender

A population pharmacokinetic analysis suggested that female patients would be expected to have higher maximum dalfampridine plasma concentration than male patients. The magnitude of these differences is small and does not necessitate any dose modification.

Renal Impairment [see Contraindications (4) and Warnings and Precautions (5.2)].

The pharmacokinetics of dalfampridine was studied in 9 male and 11 female subjects with varying degrees of renal function. Elimination of the drug is significantly correlated with the creatinine clearance. Total body clearance of dalfampridine was reduced by about 45 % in patients with mild renal impairment (CrCl 51–80 mL/min), by about 50% in patients with moderate renal impairment (CrCl = 30–50 mL/min), and by about 75% in patients with severe renal impairment (CrCl <30 mL/min). The terminal half-life of dalfampridine is about 3.3 times longer in patients with severe renal impairment but is not prolonged in patients with mild or moderate renal impairment.

Hepatic Impairment

The pharmacokinetics of dalfampridine in hepatically impaired subjects has not been studied. Since dalfampridine is primarily excreted unchanged in the urine, hepatic impairment is not expected to significantly affect dalfampridine pharmacokinetics or recommended dosing.

Race

There were too few non-Caucasians in the patient population to evaluate the effect of race.

Drug Interactions

Effects of Co-administered Drugs on Dalfampridine

Interferon

Dalfampridine kinetics were not affected by co-administration of subcutaneous injections of 8 million units interferon beta-1b.

Baclofen

Based on a population analysis, dalfampridine kinetics were not affected by baclofen.

Cimetidine

In a single-dose clinical study, 23 healthy volunteers took the OCT2 inhibitor cimetidine 400 mg every 6 hours concurrently with dalfampridine 10 mg single dose. The test-reference ratio for AUC0–∞ was 125% (90% confidence interval: 121% to 130%) due to a reduction in the clearance of dalfampridine [see Drug Interactions (7.1)].

Effects of Dalfampridine on Co-administered Drugs

In vitro data with human liver microsomes showed that dalfampridine was not a direct or time-dependent inhibitor of CYP1A2, CYP2A6, CYP2B6, CYP2C8, CYP2C9, CYP2C19, CYP2D6, or CYP3A4/5. Dalfampridine is not likely to affect the pharmacokinetics of drugs that are substrates of these enzymes.

Other in vitro studies with cultured human hepatocytes with 0.025 μM, 0.25 μM, 2.5 μM, and 25 μM dalfampridine had little or no effect on CYP1A2, CYP2B6, CYP2C9, CYP2C19, CYP2E1, or CYP3A4/5 enzyme activities. Consequently, the potential for dalfampridine to induce human hepatocytes at therapeutic concentrations is remote.

In vitro, dalfampridine is not a substrate or an inhibitor for the p-glycoprotein transporter. The pharmacokinetics of AMPYRA are unlikely to be affected by drugs that inhibit the p-glycoprotein transporter, and dalfampridine is not likely to affect the pharmacokinetics of drugs that are substrates of the p-glycoprotein transporter.

13 NONCLINICAL TOXICOLOGY

13.1 Carcinogenesis, Mutagenesis, Impairment of Fertility

Carcinogenesis

Two-year dietary carcinogenicity studies of dalfampridine were conducted in mice and rats. In mice, the doses tested (approximately 2, 12.5, and 80 mg/kg/day) were associated with plasma exposures (AUC) up to 11 times the plasma AUC in humans at the maximum recommended human dose (MRHD) of 20 mg/day. There was no evidence of drug-related carcinogenicity.

In rats, the doses tested (approximately 2, 6, and 18 mg/kg/day) were approximately 1, 3, and 9 times the MRHD on a body surface area (mg/m^2) basis. There was a significant increase in uterine polyps at the highest dose tested.

Mutagenesis

Dalfampridine was negative in in vitro (bacterial reverse mutation, mouse lymphoma tk, chromosomal aberration) and in vivo (mouse bone marrow, rat erythrocyte micronucleus) genetic toxicology assays.

Impairment of Fertility

Oral administration of dalfampridine (0, 1, 3, and 9 mg/kg/day) to male and female rats prior to and throughout mating, and continuing in females through early pregnancy (to gestation day 13) or throughout pregnancy and lactation resulted in no adverse effects on fertility. Reduced offspring viability and body weight were observed at 9 mg/kg/day. The no-effect dose for adverse effects on fertility (9 mg/kg/day) and reproductive performance (3 mg/kg/day) are 4 times and similar to, respectively, the MRHD on a mg/m^2 basis.

14 CLINICAL STUDIES

The effectiveness of AMPYRA in improving walking in patients with multiple sclerosis was evaluated in two adequate and well controlled trials involving 540 patients. Patients in these two clinical trials had a mean disease duration of 13 years and a mean Kurtzke Expanded Disability Status Scale (EDSS) score of 6.

Trial 1 was a randomized, placebo-controlled, parallel group, 21-week study (one week post screening, two-week, single-blind placebo run-in, 14-week double-blind treatment, and 4-week no treatment follow-up) in 301 patients with multiple sclerosis at 33 centers in the U.S. and Canada: 229 patients assigned to AMPYRA 10 mg twice daily and 72 patients assigned to placebo. A total of 283 patients (212 AMPYRA and 71 placebo) completed all study visits. Patient inclusion criteria included the ability to walk 25 feet in 8–45 seconds. Patient exclusion criteria included a history of seizures or evidence of epileptiform activity on a screening EEG, and onset of an MS exacerbation within 60 days.

Trial 2 was a randomized, placebo-controlled, parallel group, 14-week study (one week post-screening, two weeks of single-blind, placebo run-in, nine weeks of double-blind treatment, and two weeks of no-treatment follow-up) in 239 patients with multiple sclerosis at 39 centers in the U.S. and Canada: 120 patients assigned to 10 mg twice daily and 119 assigned to placebo. A total of 227 patients (113 AMPYRA and 114 placebo) completed all study visits. The patient inclusion and exclusion criteria used in Trial 1 were employed in Trial 2, and in addition patients with severe renal impairment were also excluded.

The primary measure of efficacy in both trials was walking speed (in feet per second) as measured by the Timed 25-foot Walk (T25FW), using a responder analysis. A responder was defined as a patient who showed faster walking speed for at least three visits out of a possible four during the double-blind period than the maximum value achieved in the five non-double-blind no treatment visits (four before the double-blind period and one after).

A significantly greater proportion of patients taking AMPYRA 10 mg twice daily were responders, compared to patients taking placebo, as measured by the T25FW (Trial 1: 34.8% vs. 8.3%; Trial 2: 42.9% vs. 9.3%). The increased response rate in the AMPYRA group was observed across all four major types of MS disease course.

During the double-blind treatment period, a significantly greater proportion of patients taking AMPYRA 10 mg twice daily had increases in walking speed of at least 10%, 20%, or 30% from baseline, compared to placebo (Figure 1 and Figure 2).

Figure 1: Average walking speed change (%) from baseline during the double-blind phase of Trial 1

Figure 2: Average walking speed change (%) from baseline during the double-blind phase of Trial 2

In Trial 1 and Trial 2, consistent improvements in walking speed were shown to be associated with improvements on a patient self-assessment of ambulatory disability, the 12-item Multiple Sclerosis Walking Scale (MSWS-12), for both drug and placebo treated patients. However, a drug-placebo difference was not established for that outcome measure.

The majority of patients in these trials (63%) were using immunomodulatory drugs (interferons, glatiramer acetate, or natalizumab), but the magnitude of improvement in walking ability was independent of concomitant treatment with these drugs. No differences in effectiveness based on degree of impairment, age, gender, or body mass index were detected. There were too few non-Caucasians in the patient population to evaluate the effect of race.

16 HOW SUPPLIED/STORAGE AND HANDLING

AMPYRA (dalfampridine) extended release tablets, 10 mg are film-coated, white to off-white, biconvex, oval shaped, non-scored tablets with flat edge. The tablets are identified by a debossed code "A10" on one side and are available in bottles of 60.

- NDC 10144-427-60 bottles of 60 tablets

STORAGE AND HANDLING

Store at 25°C (77°F). Excursions permitted 15°C to 30°C (59°F to 86°F).

17 PATIENT COUNSELING INFORMATION

Advise the patient to read the FDA-approved patient labeling (Medication Guide).

Risk of Seizures

Inform patients that AMPYRA can cause seizures, and that they must discontinue use of AMPYRA if they experience a seizure [see Warnings and Precautions (5.1)].

AMPYRA dosing

Instruct patients to take AMPYRA exactly as prescribed. Instruct patients not to take a double dose after they miss a dose, as this would increase their risk of seizure. Instruct patients not to take more than 2 tablets in a 24-hour period and to make sure that there is an approximate 12-hour interval between doses [see Dosage and Administration (2.1, 2.2)].

Anaphylaxis

Advise patients to discontinue AMPYRA and seek medical care if they develop signs and symptoms of anaphylaxis [see Warnings and Precautions (5.4)].

Effects on Driving or Using Machinery

Counsel patients that central nervous system-related adverse reactions, such as vertigo and dizziness, associated with the use of AMPYRA might impair their ability to drive or use machinery should they develop these symptoms.

Drug Interactions

Instruct patients to notify their healthcare provider prior to starting any new medication, including over-the-counter drugs.

Storage

Advise patients to store AMPYRA at 25°C (77°F), with excursions permitted to 15ºC to 30ºC (59ºF to 86ºF). Advise patients to safely throw away AMPYRA that is out of date or no longer needed.

Marketed by: Acorda Therapeutics, Inc.
Pearl River, NY 10965

AMPYRA® is a registered trademark of Acorda Therapeutics, Inc.

©2022 Acorda Therapeutics, Inc. All rights reserved.

2212427AK-1

MEDICATION GUIDE
AMPYRA® (am-PEER-ah)
(dalfampridine)
Extended Release Tablets

Read this Medication Guide before you start taking AMPYRA and each time you get a refill. There may be new information. This information does not take the place of talking with your doctor about your medical condition or your treatment.

What is the most important information I should know about AMPYRA?

AMPYRA can cause seizures.

- You could have a seizure even if you never had a seizure before.
- Your chance of having a seizure is higher if you take too much AMPYRA or if your kidneys have a mild decrease of function, which is common after age 50.
- Your doctor may do a blood test to check how well your kidneys are working, if that is not known before you start taking AMPYRA.
- Do not take AMPYRA if you have ever had a seizure.
- Before taking AMPYRA tell your doctor if you have kidney problems.
- Take AMPYRA exactly as prescribed by your doctor. See "How should I take AMPYRA?"

Stop taking AMPYRA and call your doctor right away if you have a seizure while taking AMPYRA.

What is AMPYRA?

AMPYRA is a prescription medicine used to help improve walking in adults with multiple sclerosis (MS). This was shown by an increase in walking speed.

It is not known if AMPYRA is safe or effective in children less than 18 years of age.

Who should not take AMPYRA?

Do not take AMPYRA if you:

- have ever had a seizure
- have certain types of kidney problems
- are allergic to dalfampridine (4-aminopyridine), the active ingredient in AMPYRA

What should I tell my doctor before taking AMPYRA?

Before you take AMPYRA, tell your doctor if you:

- have any other medical conditions
- are taking compounded 4-aminopyridine (fampridine, 4-AP)
- are taking any other medicines, including over-the-counter medicines such as cimetidine
- are pregnant or plan to become pregnant. It is not known if AMPYRA will harm your unborn baby.
- are breast-feeding or plan to breast-feed. It is not known if AMPYRA passes into your breast milk. Talk with your healthcare provider about the best way to feed your baby if you take AMPYRA.

Tell your doctor about all the medicines you take, including prescription and non-prescription medicines, vitamins and herbal supplements.

Know the medicines you take. Keep a list of them and show it to your doctor and pharmacist when you get a new medicine.

How should I take AMPYRA?

- Take AMPYRA exactly as your doctor tells you to take it. Do not change your dose of AMPYRA.
- Take one tablet of AMPYRA 2 times each day about 12 hours apart. Do not take more than 2 tablets of AMPYRA in a 24-hour period.
- Take AMPYRA tablets whole. Do not break, crush, chew or dissolve AMPYRA tablets before swallowing. If you cannot swallow AMPYRA tablets whole, tell your doctor.
- AMPYRA is released slowly over time. If the tablet is broken, the medicine may be released too fast. This can raise your chance of having a seizure.
- AMPYRA can be taken with or without food.
- If you miss a dose of AMPYRA, do not make up the missed dose. Do not take 2 doses at the same time. Take your next dose at your regular scheduled time.
- If you take too much AMPYRA, call your doctor or go to the nearest hospital emergency room right away.
- Do not take AMPYRA together with other aminopyridine medications, including compounded 4-AP (sometimes called 4-aminopyridine, fampridine).

What should I avoid while taking AMPYRA?

AMPYRA may cause dizziness or vertigo. If you have these symptoms, do not drive, operate machinery, or do other dangerous activities.

What are the possible side effects of AMPYRA?

AMPYRA may cause serious side effects, including:

- serious allergic reactions. Stop taking AMPYRA and call your doctor right away or get emergency medical help if you have:
  - shortness of breath or trouble breathing
  - swelling of your throat or tongue
  - hives

See "What is the most important information I should know about AMPYRA?"

The most common side effects of AMPYRA include:

- urinary tract infection
- trouble sleeping (insomnia)
- dizziness
- headache
- nausea
- weakness
- back pain
- problems with balance
- multiple sclerosis relapse
- burning, tingling or itching of your skin
- irritation in your nose and throat
- constipation
- indigestion
- pain in your throat

Tell your doctor if you have any side effect that bothers you or that does not go away.

These are not all the possible side effects of AMPYRA. For more information, ask your doctor or pharmacist.

Call your doctor for medical advice about side effects. You may report side effects to the FDA at 1-800-FDA-1088.

How should I store AMPYRA?

- Store AMPYRA at 59ºF to 86ºF (15ºC to 30ºC).
- Safely throw away AMPYRA that is out of date or no longer needed.

Keep AMPYRA and all medicines out of the reach of children.

General Information about the safe and effective use of AMPYRA

Medicines are sometimes prescribed for purposes other than those listed in a Medication Guide. Do not use AMPYRA for a condition for which it was not prescribed. Do not give AMPYRA to other people, even if they have the same symptoms that you have. It may harm them.

This Medication Guide summarizes the most important information about AMPYRA. If you would like more information, talk with your doctor. You can ask your pharmacist or doctor for information about AMPYRA that is written for health professionals.

For more information, go to www.AMPYRA.com or call 1-800-367-5109.

What are the ingredients in AMPYRA?

Active ingredient: dalfampridine (previously called fampridine)

Inactive ingredients: colloidal silicon dioxide, hydroxypropyl methylcellulose, magnesium stearate, microcrystalline cellulose, polyethylene glycol, and titanium dioxide.

Marketed by: Acorda Therapeutics, Inc.
Pearl River, NY 10965

Revised 06/2022

This Medication Guide has been approved by the U.S. Food and Drug Administration.

AMPYRA® is a registered trademark of Acorda Therapeutics, Inc.

©2022 Acorda Therapeutics, Inc. All rights reserved.

2212427AK-1

PRINCIPAL DISPLAY PANEL - 10 mg Tablet Label

ampyra®

(dalfampridine)

Extended Release
Tablets

Rx ONLY

10 mg

PHARMACIST: Dispense the accompanying
Medication Guide to each patient

60 tablets